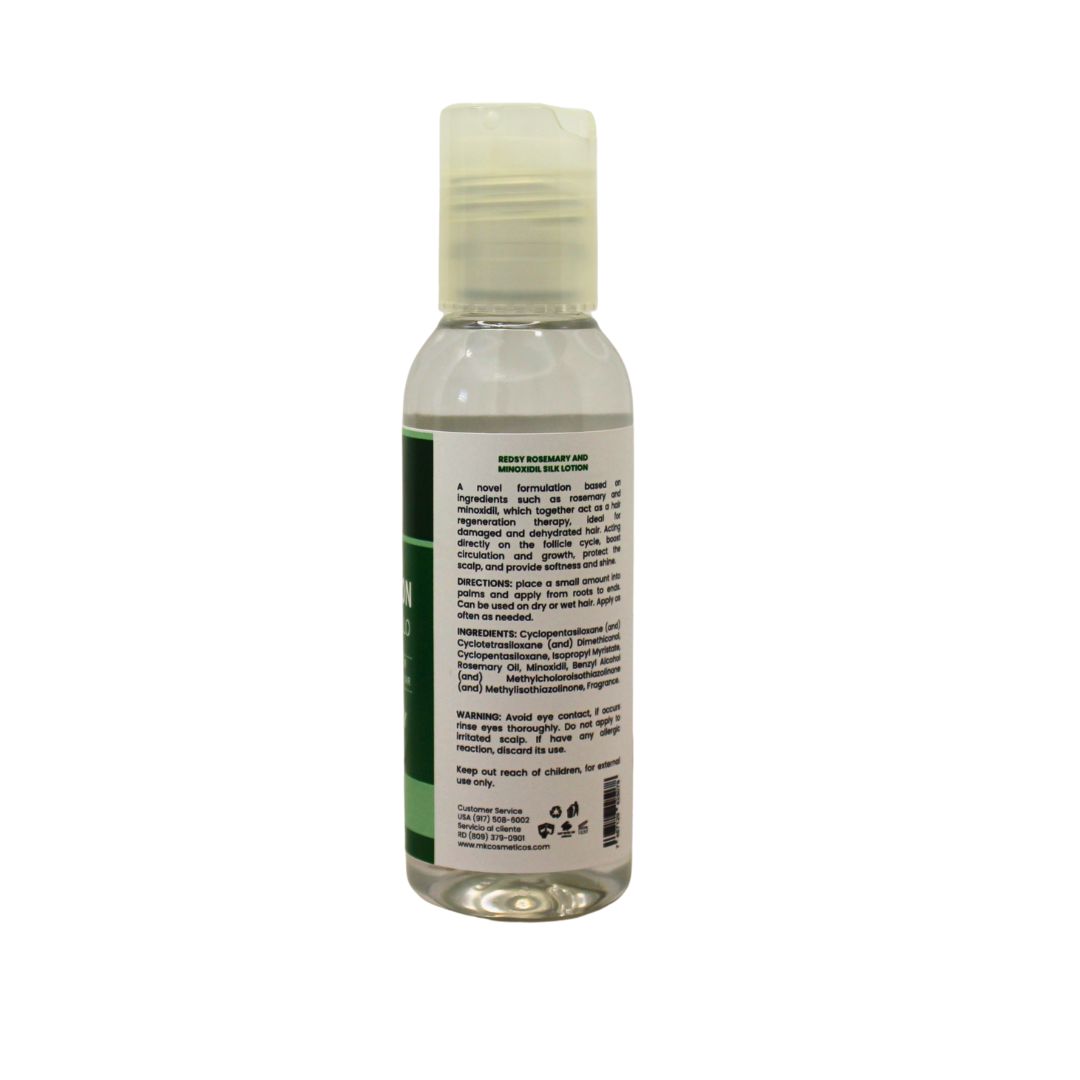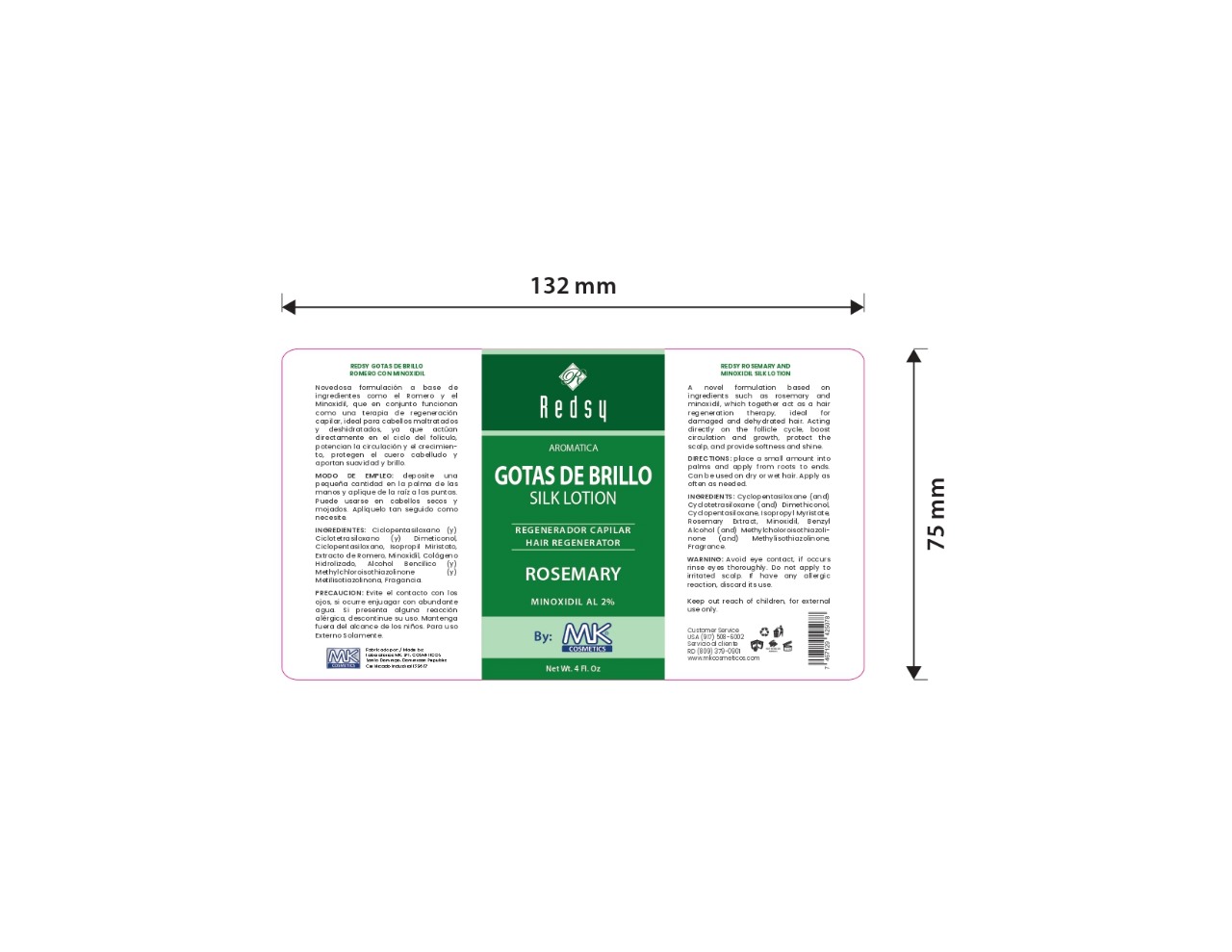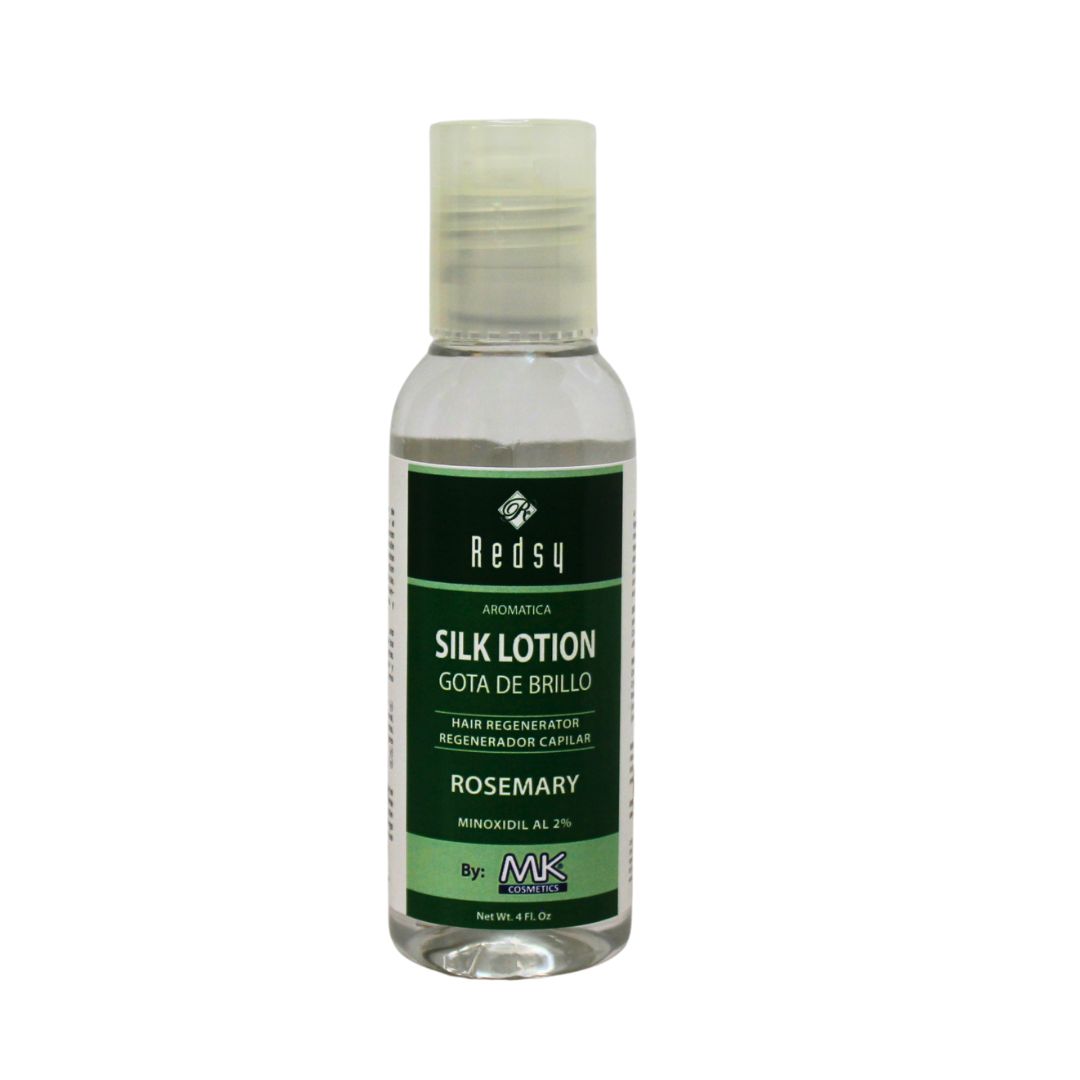 DRUG LABEL: aromatica hair gota de brillo romero con minoxidil
NDC: 87022-015 | Form: LIQUID
Manufacturer: LABORATORIO MK SRL
Category: otc | Type: HUMAN OTC DRUG LABEL
Date: 20251002

ACTIVE INGREDIENTS: MINOXIDIL 2 mg/117.6 mL
INACTIVE INGREDIENTS: BENZYL ALCOHOL; METHYLCHLOROISOTHIAZOLINONE; CYCLOTETRASILOXANE; CYCLOPENTASILOXANE AND DIMETHICONOL (6000 CP); ISOPROPYL MYRISTATE; METHYLISOTHIAZOLINONE; ROSEMARY OIL; CYCLOPENTASILOXANE

INDICATIONS AND USAGE

place a small amount into palms and apply from roots to ends. Can be used on dry or wet hair. Apply as often as needed.

INACTIVE INGREDIENT

Cyclopentasiloxane (and) Cyclotetrasiloxane (and) Dimethiconol, Cyclopentasiloxane, Isopropyl Myristate, Rosemary Extract, Benzyl Alcohol (and) Methylcholoroisothiazolinone (and) Methylisothiazolinone, Fragrance.

WARNINGS

Avoid eye contact, if occurs rinse eyes thoroughly with water. If develop any allergic reaction, discontinue its use.

INFORMATION FOR OWNERS/CAREGIVERS

Customer Service USA (917)508-6002

Customer Service RD (809)379-0900

www.mkcosmeticos.com

DOSAGE AND ADMINISTRATION

place a small amount into palms and apply from roots to ends. Can be used on dry or wet hair. Apply as often as needed.

KEEP OUT OF REACH OF CHILDREN

Keep out reach of children. For external use only.

PURPOSE

aromatica hair regenerator

PACKAGE LABEL

aromatica silk lotion hair regenerator rosemary with minoxidil